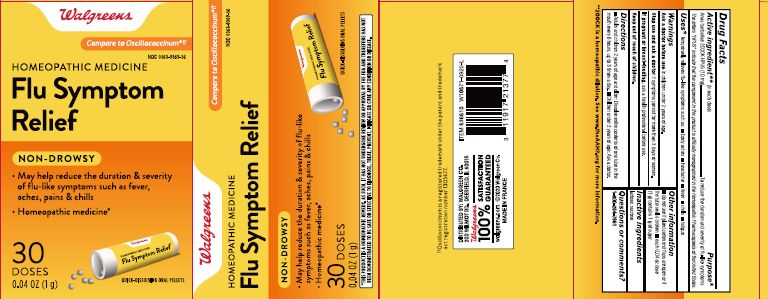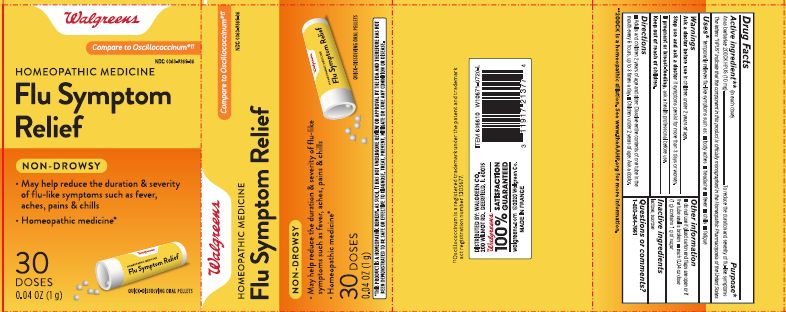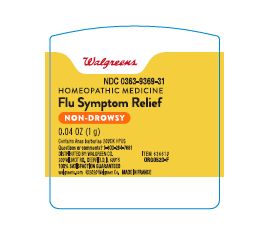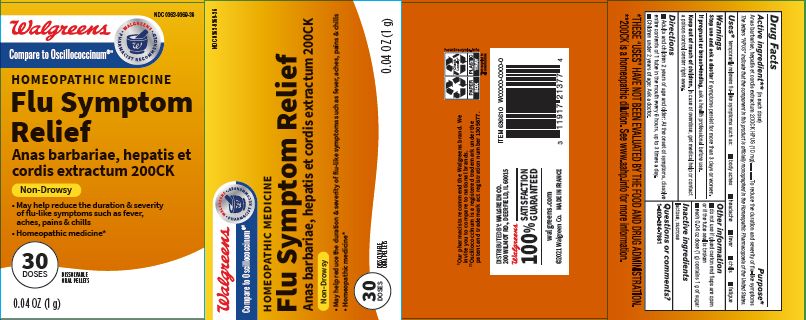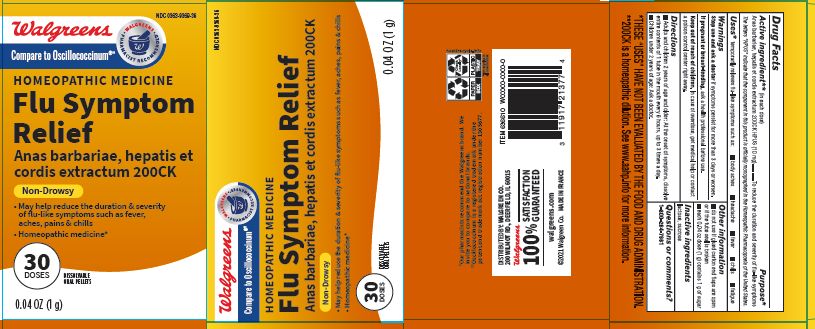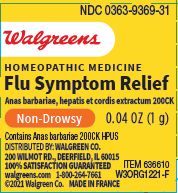 DRUG LABEL: Flu Symptom Relief
NDC: 0363-9369 | Form: PELLET
Manufacturer: Walgreens Co.
Category: homeopathic | Type: HUMAN OTC DRUG LABEL
Date: 20230502

ACTIVE INGREDIENTS: CAIRINA MOSCHATA HEART/LIVER AUTOLYSATE 200 [kp_C]/200 [kp_C]
INACTIVE INGREDIENTS: LACTOSE, UNSPECIFIED FORM; SUCROSE

Flu Symptom Relief

ACTIVE INGREDIENT

Anas barbariae, hepatis et cordis extractum 200CK HPUS (10mg) **(in each dose)

PURPOSE

Anas barbarie, hepatis et cordis extractum 200CK HPUS (10 mg) ..... To reduce the duration and severity of flu-like symptoms*

INDICATIONS AND USAGE

Temporarily relieves flu-like symptoms such as: body aches, headache, fever, chills, fatigue*

Stop use and ask a doctor if symptoms persist for more than 3 days or worsen.

PREGNANCY OR BREAST FEEDING

If pregnant or breast-feeding, ask a health professional before use.

Keep out of reach of children. In case of overdose, get medical help or contact a poison control center right away.

DOSAGE AND ADMINISTRATION

Adults and children 2 years of age and older: At the onset of symptoms, dissolve entire contents of 1 tube in the mouth every 6 hours, up to 3 times a day.

Children under 2 years of age: Ask a doctor.

Do not use if glued carton and flaps are open or if the tube seal is broken

Each 0.04 oz dose (1 g) contains 1 g of sugar

30 doses

Dissolvable oral pellets

** 200CK is a homeopathic dilution. See www.AAHP.info for more information.

Non-drowsy

*THESE "USES" HAVE NOT BEEN FDA EVALUATED BY THE FOOD AND DRUG ADMINISTRATION.

†† Oscillococcinum is a registered trademark under the patent and trademark act registration number 1305677.

The letters "HPUS" indicate that the components in this product are officially monographed in the Homeopathic Pharmacopoeia of the United States.

May help reduce the duration & severity of flu-like symptoms such as fever, aches, pain & chills

Homeopathic medicine*

Distributed By: Walgreen Co. 200 Milmot Rd, Deerfield, IL 60015

walgreens.com

Made in France

INACTIVE INGREDIENT

lactose, sucrose

QUESTIONS

1-800-264-7661